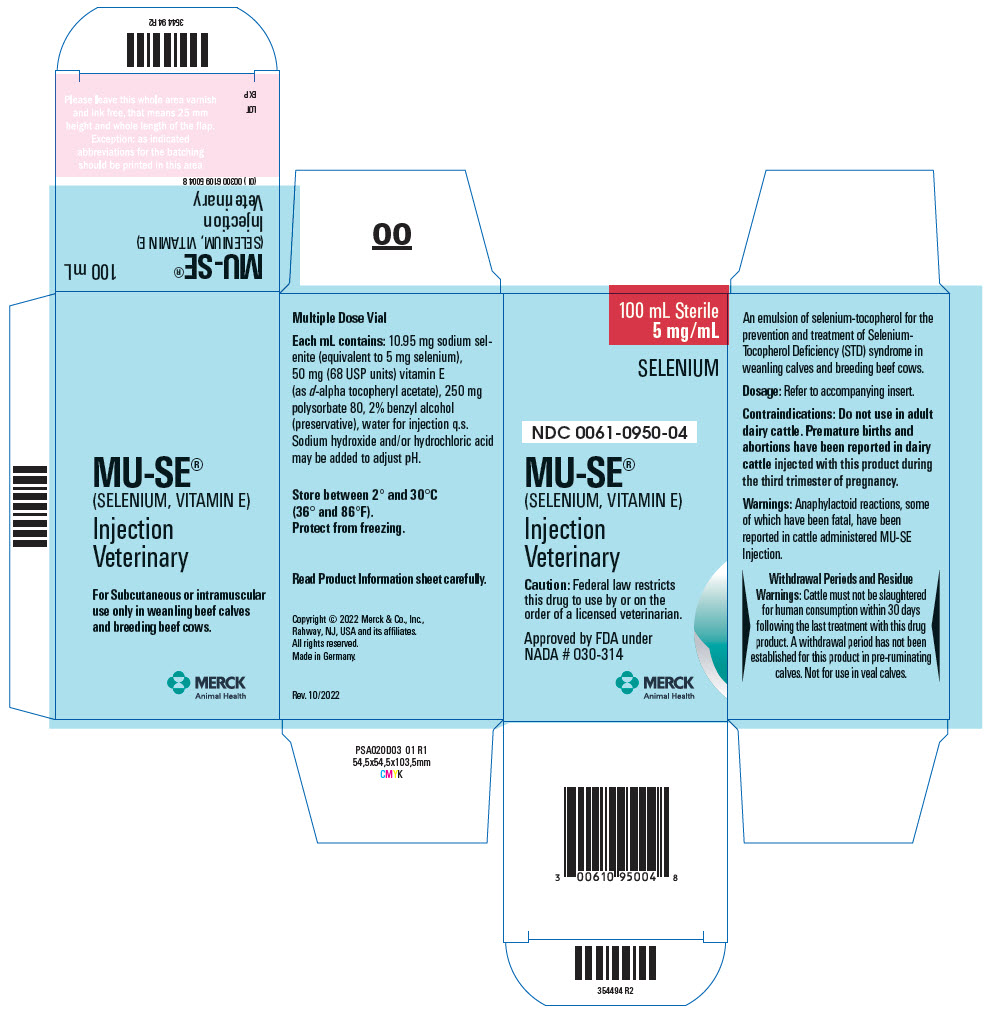 DRUG LABEL: MU-SE
NDC: 0061-0950 | Form: INJECTION, SOLUTION
Manufacturer: Merck Sharp & Dohme Corp.
Category: animal | Type: PRESCRIPTION ANIMAL DRUG LABEL
Date: 20241112

ACTIVE INGREDIENTS: SODIUM SELENITE 5 mg/1 mL; .ALPHA.-TOCOPHEROL ACETATE, D- 68 [USP'U]/1 mL

MU-SE®
(SELENIUM, VITAMIN E)
Injection

Approved by FDA under NADA # 030-314

PRODUCT INFORMATION

FOR VETERINARY USE ONLY

For Subcutaneous or intramuscular use only in weanling beef calves and breeding beef cows.

CAUTION Federal law restricts this drug to use by or on the order of a licensed veterinarian.

DESCRIPTION

DESCRIPTION MU-SE (selenium, vitamin E) is an emulsion of selenium-tocopherol for the prevention and treatment of Selenium-Tocopherol Deficiency (STD) syndrome in weanling calves and breeding beef cattle. Each mL contains: 10.95 mg sodium selenite (equivalent to 5 mg selenium), 50 mg (68 USP units) vitamin E (as d-alpha tocopheryl acetate), 250 mg polysorbate 80, 2% benzyl alcohol (preservative), water for injection q.s. Sodium hydroxide and/or hydrochloric acid may be added to adjust pH.

MECHANISM OF ACTION

ACTIONS It has been demonstrated that selenium and tocopherol exert physiological effects and that these effects are intertwined with sulfur metabolism. Additionally, tocopherol appears to have a significant role in the oxidation process, thus suggesting an interrelationship between selenium and tocopherol in overcoming sulfur-induced depletion and restoring normal metabolism. Although oral ingestion of adequate amounts of selenium and tocopherol would seemingly restore normal metabolism, it is apparent that the presence of sulfur and, perhaps, other factors interfere during the digestive process with proper utilization of selenium and tocopherol. When selenium and tocopherol are injected, they bypass the digestive process and exert their full metabolic effects promptly on cell metabolism. Anti-inflammatory action has been demonstrated by selenium-tocopherol in the Selye Pouch Technique and experimentally induced polyarthritis study in rats.

VETERINARY INDICATIONS

INDICATIONS MU-SE (selenium, vitamin E) is recommended for the prevention and treatment of STD syndrome in weanling calves and breeding beef cattle. Clinical signs are: stiffness and lameness; chronic, persistent diarrhea; unthriftiness; abortions and/or weak premature calves.

CONTRAINDICATIONS

CONTRAINDICATION Do not use in adult dairy cattle. Premature births and abortions have been reported in dairy cattle injected with this product during the third trimester of pregnancy.

WARNINGS

WARNINGS Anaphylactoid reactions, some of which have been fatal, have been reported in cattle administered the MU-SE product. Signs include excitement, sweating, trembling, ataxia, respiratory distress, and cardiac dysfunction.

Withdrawal Periods and Residue Warnings: Cattle must not be slaughtered for human consumption within 30 days following the last treatment with this drug product. A withdrawal period has not been established for this product in pre-ruminating calves. Not for use in veal calves.

DOSAGE AND ADMINISTRATION Inject subcutaneously or intramuscularly. Weanling calves: 1 mL per 200 pounds of body weight. Breeding beef cows: 1 mL per 200 pounds of body weight during the middle third of pregnancy, and 30 days before calving.

CAUTION Selenium is toxic if administered in excess. A fixed dose schedule is therefore important (read package insert for each selenium-tocopherol product carefully before using).

PRECAUTIONS

PRECAUTIONS Selenium-Tocopherol Deficiency (STD) syndrome produces a variety and complexity of symptoms often interfering with a proper diagnosis. Even in selenium deficient areas there are other disease conditions which produce similar clinical signs. It is imperative that all these conditions be carefully considered prior to treatment of STD syndrome. Serum selenium levels, elevated SGOT, and creatine levels may serve as aids in arriving at a diagnosis of STD, when associated with other indices.

Important Use only the selenium-tocopherol product recommended for each species. Each formulation is designed for the species indicated to produce the maximum efficacy and safety.

HOW SUPPLIED 100 mL sterile, multiple dose vial.

STORAGE AND HANDLING

STORAGE Store between 2° and 30°C (36° and 86°F). Protect from freezing.

Rev. 10/2022

Copyright © 2022 Merck & Co., Inc., Rahway, NJ, USA and its affiliates. All rights reserved.
Made in Germany.

MERCK
Animal Health

399309 R2

PRINCIPAL DISPLAY PANEL - 100 mL Vial Carton

100 mL Sterile
5 mg/mL

SELENIUM

NDC 0061-0950-04

MU-SE®
(SELENIUM, VITAMIN E)

Injection
Veterinary

Caution: Federal law restricts
this drug to use by or on the
order of a licensed veterinarian.

Approved by FDA under
NADA # 030-314

MERCK
Animal Health